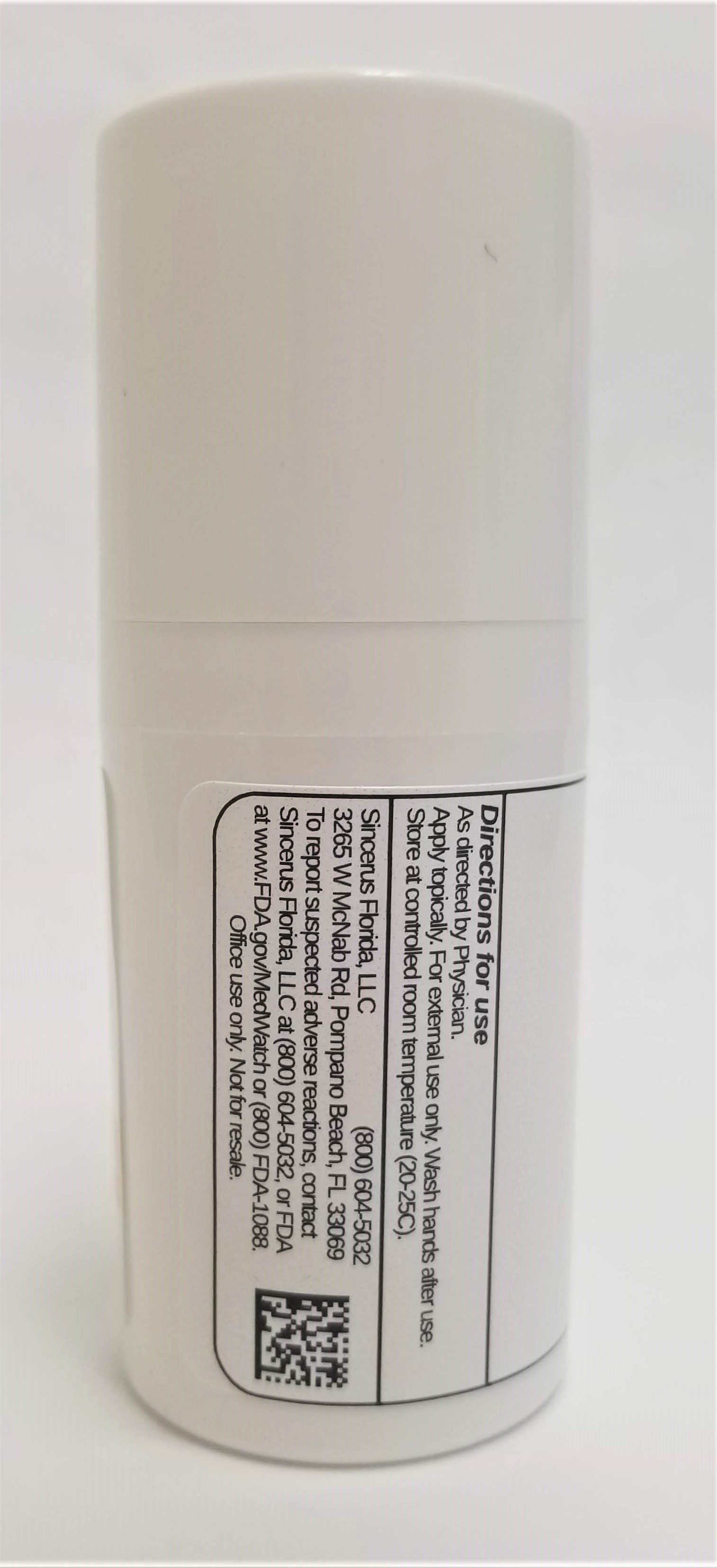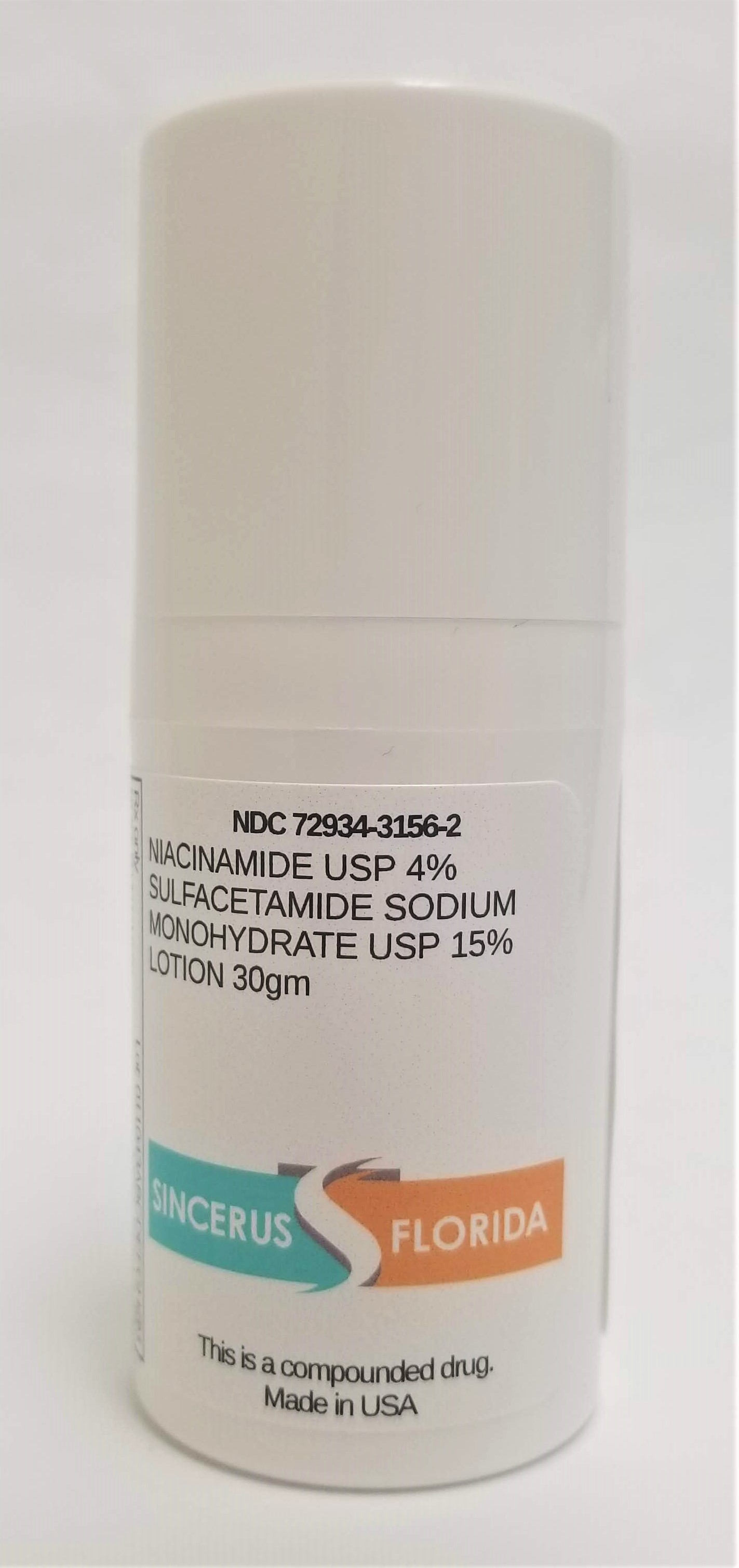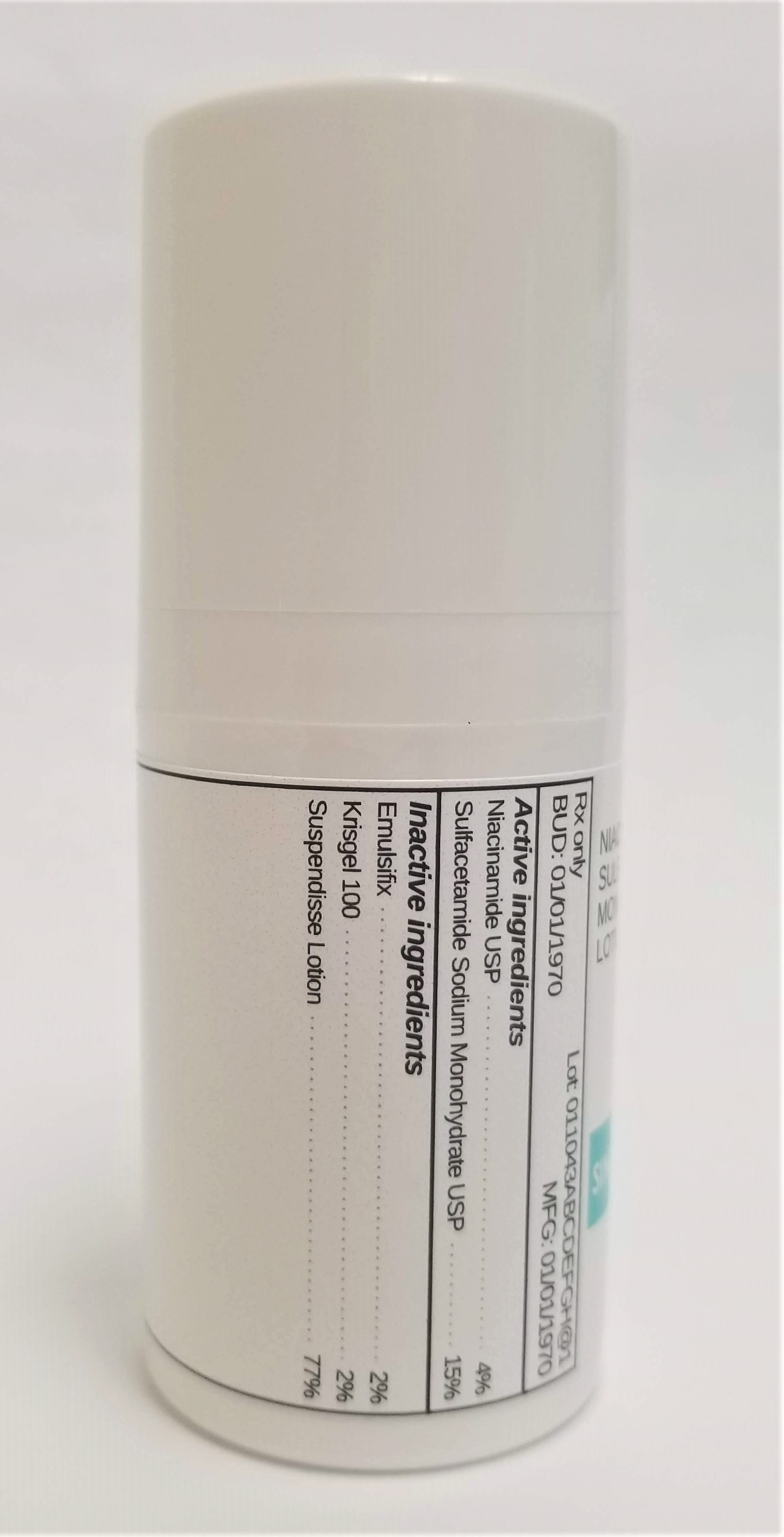 DRUG LABEL: NIACINAMIDE 4% / SODIUM SULFACETAMIDE MONOHYDRATE 15%
NDC: 72934-3156 | Form: LOTION
Manufacturer: Sincerus Florida, LLC
Category: prescription | Type: HUMAN PRESCRIPTION DRUG LABEL
Date: 20190510

ACTIVE INGREDIENTS: NIACINAMIDE 4 g/100 g; SULFACETAMIDE SODIUM 15 g/100 g

NIACINAMIDE 4% / SODIUM SULFACETAMIDE MONOHYDRATE 15%